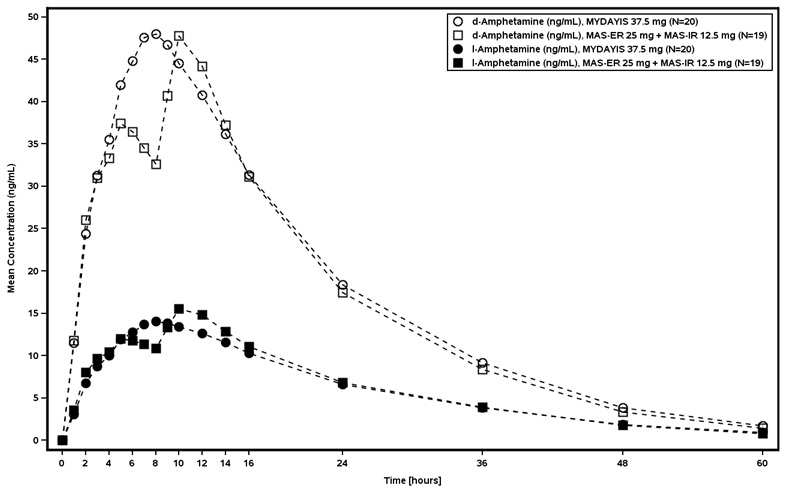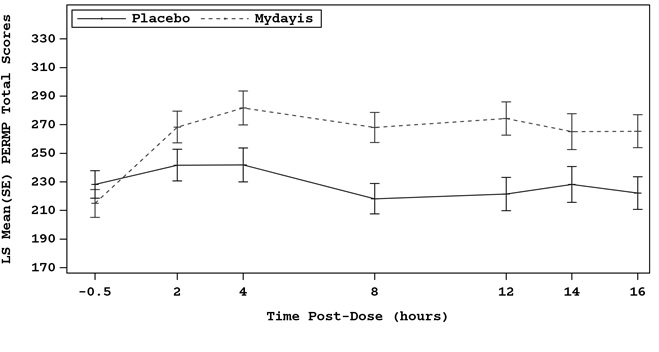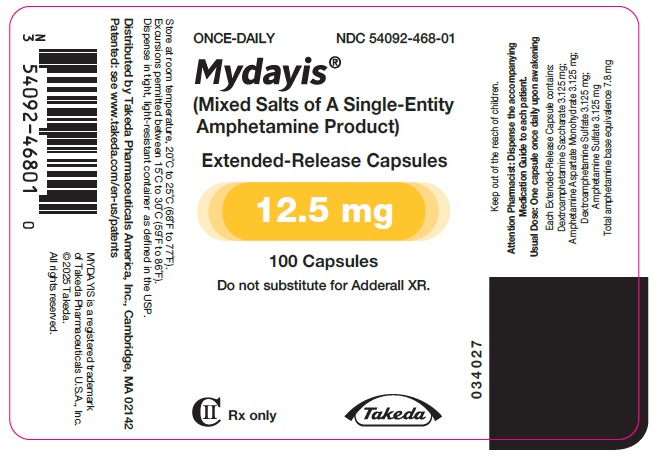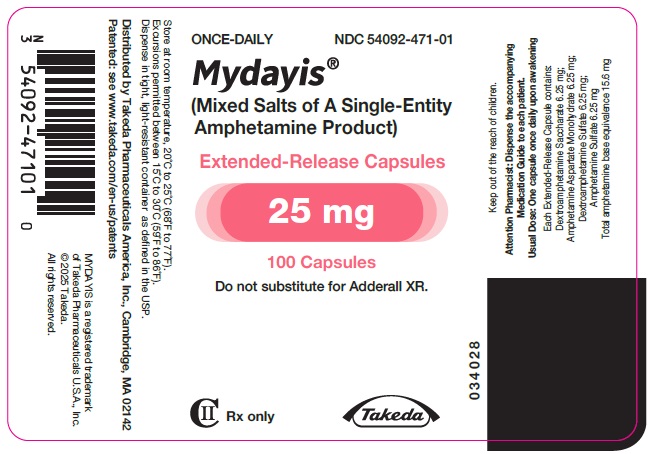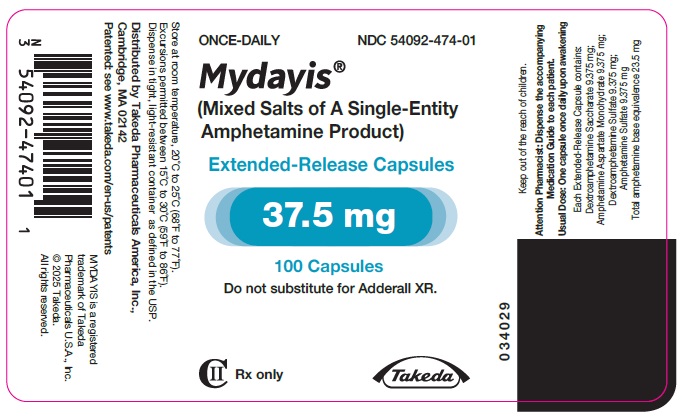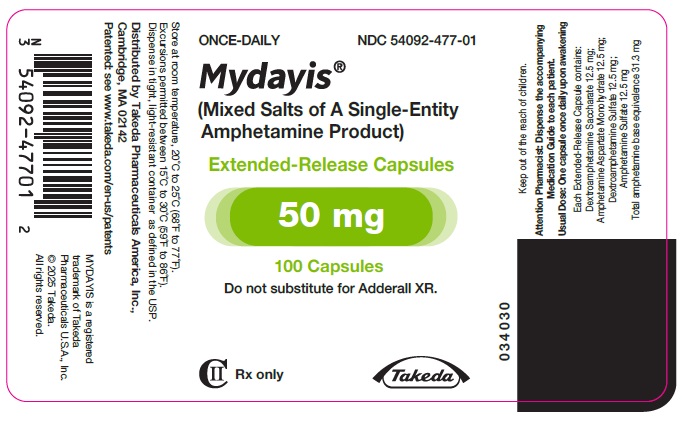 DRUG LABEL: MYDAYIS
NDC: 54092-468 | Form: CAPSULE, EXTENDED RELEASE
Manufacturer: Takeda Pharmaceuticals America, Inc.
Category: prescription | Type: HUMAN PRESCRIPTION DRUG LABEL
Date: 20250310
DEA Schedule: CII

ACTIVE INGREDIENTS: DEXTROAMPHETAMINE SULFATE 3.125 mg/1 1; DEXTROAMPHETAMINE SACCHARATE 3.125 mg/1 1; AMPHETAMINE ASPARTATE MONOHYDRATE 3.125 mg/1 1; AMPHETAMINE SULFATE 3.125 mg/1 1
INACTIVE INGREDIENTS: GELATIN, UNSPECIFIED; HYPROMELLOSE, UNSPECIFIED; METHACRYLIC ACID AND ETHYL ACRYLATE COPOLYMER; POLY(METHYL ACRYLATE-CO-METHYL METHACRYLATE-CO-METHACRYLIC ACID 7:3:1; 280000 MW); SUCROSE; TALC; TRIETHYL CITRATE; FD&C BLUE NO. 2; FERRIC OXIDE YELLOW; TITANIUM DIOXIDE

HIGHLIGHTS OF PRESCRIBING INFORMATION

These highlights do not include all the information needed to use MYDAYIS safely and effectively. See full prescribing information for MYDAYIS.
MYDAYIS® (mixed salts of a single-entity amphetamine product) extended-release capsules, for oral use, CII
Initial U.S. Approval: 2001

WARNING: ABUSE, MISUSE, AND ADDICTION

See full prescribing information for complete boxed warning.

MYDAYIS has a high potential for abuse and misuse, which can lead to the development of a substance use disorder, including addiction. Misuse and abuse of CNS stimulants, including MYDAYIS, can result in overdose and death (5.1, 9.2, 10):

- Before prescribing MYDAYIS, assess each patient’s risk for abuse, misuse, and addiction.
- Educate patients and their families about these risks, proper storage of the drug, and proper disposal of any unused drug.
- Throughout treatment, reassess each patient’s risk and frequently monitor for signs and symptoms of abuse, misuse, and addiction.

1 INDICATIONS AND USAGE

MYDAYIS is a central nervous system (CNS) stimulant indicated for the treatment of Attention Deficit Hyperactivity Disorder (ADHD) in patients 13 years and older. (1)

Limitations of Use:

Pediatric patients 12 years and younger experienced higher plasma exposure than patients 13 years and older at the same dose and experienced higher rates of adverse reactions, mainly insomnia and decreased appetite. (8.4)

2 DOSAGE AND ADMINISTRATION

- MYDAYIS should be administered once daily upon awakening.

 | Recommended Starting Dose | Titration Schedule | Maximum Daily Dose
Adults | 12.5 mg | 12.5 mg weekly | 50 mg
Pediatrics (13 to 17) | 12.5 mg | 12.5 mg weekly | 25 mg

- In adult patients with severe renal impairment the maximum dose should not exceed 25 mg daily. Use in adult patients with ESRD is not recommended. (2.6, 8.6)
- The maximum dose in pediatric patients with severe renal impairment is 12.5 mg daily. Use in pediatric patients with ESRD is not recommended. (2.6, 8.6)
- Patients are advised to take consistently either with or without food. (2.2)
- Administer upon awakening because the effects may last up to 16 hours and there is the potential for insomnia. (2.2)
- Prior to treatment, assess for presence of cardiac disease. (2.1)
- To avoid substitution errors and overdosage, do not substitute for other amphetamine products on a milligram-per-milligram basis because of different amphetamine base compositions and differing pharmacokinetic profiles. (2.7)

3 DOSAGE FORMS AND STRENGTHS

Extended-release capsules: 12.5 mg, 25 mg, 37.5 mg, 50 mg (3)

4 CONTRAINDICATIONS

- Known hypersensitivity to amphetamine products or other ingredients in MYDAYIS. (4)
- Use with monoamine oxidase (MAO) inhibitors, or within 14 days of the last MAO inhibitor dose. (4, 7.1)

5 WARNINGS AND PRECAUTIONS

- Risks to Patients with Serious Cardiac Disease: Avoid use in patients with known structural cardiac abnormalities, cardiomyopathy, serious cardiac arrhythmia, coronary artery disease, or other serious cardiac disease. (5.2)
- Increased Blood Pressure and Heart Rate: Monitor blood pressure and pulse. (5.3)
- Psychiatric Adverse Reactions: Prior to initiating MYDAYIS, screen patients for risk factors for developing a manic episode. If new psychotic or manic symptoms occur, consider discontinuing MYDAYIS. (5.4)
- Long-Term Suppression of Growth in Pediatric Patients: Closely monitor growth (height and weight) in pediatric patients. Pediatric patients not growing or gaining height or weight as expected may need to have their treatment interrupted. (5.5)
- Peripheral Vasculopathy, Including Raynaud’s Phenomenon: Careful observation for digital changes is necessary during MYDAYIS treatment. Further clinical evaluation (e.g., rheumatology referral) may be appropriate for patients who develop signs or symptoms of peripheral vasculopathy. (5.6)
- Seizures: May lower the convulsive threshold. If a seizure occurs, discontinue MYDAYIS. (5.7)
- Serotonin Syndrome: Increased risk when coadministered with serotonergic agents (e.g., SSRIs, SNRIs, triptans), but also during overdosage situations. If it occurs, discontinue MYDAYIS and initiate supportive treatment. (5.8)
- Motor and Verbal Tics, and Worsening of Tourette’s Syndrome: Before initiating MYDAYIS, assess the family history and clinically evaluate patients for tics or Tourette’s syndrome. Regularly monitor patients for the emergence or worsening of tics or Tourette’s syndrome. Discontinue treatment if clinically appropriate. (5.10)

6 ADVERSE REACTIONS

Most common adverse reactions in patients with ADHD (incidence ≥5% and at a rate at least twice placebo) are:

- Pediatrics (13 years and older): insomnia, decreased appetite, decreased weight, irritability, and nausea. (6.1)
- Adults: insomnia, decreased appetite, decreased weight, dry mouth, increased heart rate, and anxiety. (6.1)

To report SUSPECTED ADVERSE REACTIONS, contact Takeda Pharmaceuticals U.S.A., Inc. at 1-877-TAKEDA-7 (1-877-825-3327) or FDA at 1-800-FDA-1088 or www.fda.gov/medwatch.

7 DRUG INTERACTIONS

Acidifying and Alkalinizing Agents: Agents that alter GI and urinary pH can alter blood levels of amphetamine. Acidifying agents (GI and urinary) decrease amphetamine blood levels, while alkalinizing agents (GI and urinary) increase amphetamine blood levels. Adjust MYDAYIS dosage accordingly. (2.5, 7.1)

8 USE IN SPECIFIC POPULATIONS

- Pregnancy: Based on animal data, may cause fetal harm. (8.1)
- Lactation: Breastfeeding not recommended. (8.2)
- Pediatric: Safety and effectiveness have not been established in pediatric patients ages 12 years and younger. (8.4)
- Renal Impairment: Dose adjustment is needed in patients with severe renal insufficiency. Use of MYDAYIS in patients with ESRD is not recommended. (2.6, 8.6)

FULL PRESCRIBING INFORMATION

WARNING: ABUSE, MISUSE, AND ADDICTION

MYDAYIS has a high potential for abuse and misuse, which can lead to the development of a substance use disorder, including addiction. Misuse and abuse of CNS stimulants, including MYDAYIS, can result in overdose and death [see Overdosage (10)], and this risk is increased with higher doses or unapproved methods of administration, such as snorting or injection.

Before prescribing MYDAYIS, assess each patient’s risk for abuse, misuse, and addiction. Educate patients and their families about these risks, proper storage of the drug, and proper disposal of any unused drug. Throughout MYDAYIS treatment, reassess each patient’s risk of abuse, misuse, and addiction and frequently monitor for signs and symptoms of abuse, misuse, and addiction [see Warnings and Precautions (5.1), Drug Abuse and Dependence (9.2)].

1 INDICATIONS AND USAGE

MYDAYIS is indicated for the treatment of Attention Deficit Hyperactivity Disorder (ADHD) in patients 13 years and older [see Clinical Studies (14)].

Limitations of Use:

Pediatric patients 12 years and younger experienced higher plasma exposure than patients 13 years and older at the same dose, and experienced higher rates of adverse reactions, mainly insomnia and decreased appetite [see Use in Specific Populations (8.4)].

2 DOSAGE AND ADMINISTRATION

2.1 Pretreatment Screening

Prior to treating patients with MYDAYIS, assess:

- for the presence of cardiac disease (i.e., perform a careful history, family history of sudden death or ventricular arrhythmia, and physical exam) [see Warnings and Precautions (5.2)]
- the family history and clinically evaluate patients for motor or verbal tics or Tourette’s syndrome before initiating MYDAYIS [see Warnings and Precautions (5.10)]

2.2 General Administration Information

Because the effects of MYDAYIS may last up to 16 hours and there is potential for insomnia, administer once daily in the morning upon awakening. In the event of a missed dose, do not administer later in the day. Do not administer additional medication to make up for the missed dose [see Adverse Reactions (6.1), Clinical Studies (14)].

2.3 Administration Instructions

Administer MYDAYIS orally with or without food. Advise patients to take MYDAYIS consistently either with food or without food [see Clinical Pharmacology (12.3)].

MYDAYIS may be administered in one of the following ways:

- Swallow MYDAYIS capsules whole, or
- Open capsule and sprinkle the entire contents over a spoonful of applesauce. The sprinkled applesauce should be consumed immediately; it should not be stored. Patients should take the sprinkled applesauce in its entirety without chewing.
- The dose of a single capsule should not be divided.

2.4 Recommended Dosage

Adults (18 to 55 years)

The recommended starting dose of MYDAYIS is 12.5 mg once daily in the morning upon awakening. Initial doses of 25 mg once daily may be considered for some patients. Dosage may be adjusted in increments of 12.5 mg no sooner than weekly, up to a maximum dose of 50 mg once daily, based on the therapeutic needs and response of the patient. Doses above 50 mg daily have shown no additional clinically meaningful benefit.

Pediatric Patients (13 to 17 years)

The recommended starting dose is 12.5 mg once daily in the morning upon awakening. Dosage may be adjusted in increments of 12.5 mg no sooner than weekly, up to a recommended maximum dose of 25 mg once daily. The dose should be individualized according to the needs and response of the patient. Doses higher than 25 mg have not been evaluated in clinical trials in pediatric patients.

2.5 Dosage Modifications Due to Drug Interactions

Agents that alter gastrointestinal and urinary pH can impact urinary excretion and alter blood levels of amphetamine. Acidifying agents (e.g., ascorbic acid) decrease blood levels, while alkalinizing agents (e.g., sodium bicarbonate) increase blood levels. Adjust MYDAYIS dosage accordingly [see Drug Interactions (7.1)].

2.6 Dosage in Patients with Renal Impairment

In adult patients with severe renal impairment (GFR between 15 to <30 mL/min/1.73 m^2), the recommended starting dose of MYDAYIS is 12.5 mg daily with a maximum recommended dose of 25 mg daily. MYDAYIS is not recommended for use in patients with end stage renal disease (ESRD <15 mL/min/1.73 m^2). In pediatric patients (13 to 17 years) with severe renal impairment, the maximum dose is 12.5 mg, if tolerated [see Use in Specific Populations (8.6), Clinical Pharmacology (12.3)].

2.7 Switching From Other Amphetamine Products

For patients switching from another medication or any other amphetamine products, discontinue that treatment, and titrate with MYDAYIS using the titration schedule [see Dosage and Administration (2.4)].

Do not substitute for other amphetamine products on a milligram-per-milligram basis because of different amphetamine base compositions and differing pharmacokinetic profiles [see Warnings and Precautions (5.9), Description (11), Clinical Pharmacology (12.3)].

3 DOSAGE FORMS AND STRENGTHS

- Extended-release capsules 12.5 mg: green body/green cap (imprinted with SHIRE 465 and 12.5 mg)
- Extended-release capsules 25 mg: ivory body/green cap (imprinted with SHIRE 465 and 25 mg)
- Extended-release capsules 37.5 mg: ivory body/light caramel cap (imprinted with SHIRE 465 and 37.5 mg)
- Extended-release capsules 50 mg: ivory body/purple cap (imprinted with SHIRE 465 and 50 mg)

4 CONTRAINDICATIONS

MYDAYIS is contraindicated in patients with:

- Known hypersensitivity to amphetamine, or other components of MYDAYIS. Hypersensitivity reactions such as angioedema and anaphylactic reactions have been reported in patients treated with other amphetamine products [see Adverse Reactions (6.2)].
- Concomitant treatment with monoamine oxidase inhibitors (MAOIs), and also within 14 days following discontinuation of treatment with a monoamine oxidase inhibitor, because of an increased risk of hypertensive crisis [see Drug Interactions (7.1)].

5 WARNINGS AND PRECAUTIONS

5.1 Abuse, Misuse, and Addiction

MYDAYIS has a high potential for abuse and misuse. The use of MYDAYIS exposes individuals to the risks of abuse and misuse, which can lead to the development of a substance use disorder, including addiction. MYDAYIS can be diverted for non-medical use into illicit channels or distribution [see Drug Abuse and Dependence (9.2)]. Misuse and abuse of CNS stimulants, including MYDAYIS, can result in overdose and death [see Overdosage (10)], and this risk is increased with higher doses or unapproved methods of administration, such as snorting or injection.

Before prescribing MYDAYIS, assess each patient’s risk for abuse, misuse, and addiction. Educate patients and their families about these risks and proper disposal of any unused drug. Advise patients to store MYDAYIS in a safe place, preferably locked, and instruct patients to not give MYDAYIS to anyone else. Throughout MYDAYIS treatment, reassess each patient’s risk of abuse, misuse, and addiction and frequently monitor for signs and symptoms of abuse, misuse, and addiction.

5.2 Risks to Patients with Serious Cardiac Disease

Sudden death has been reported in patients with structural cardiac abnormalities or other serious cardiac disease who were treated with CNS stimulants at the recommended ADHD dosage.

Avoid MYDAYIS use in patients with known structural cardiac abnormalities, cardiomyopathy, serious cardiac arrhythmia, coronary artery disease, or other serious cardiac disease.

5.3 Increased Blood Pressure and Heart Rate

CNS stimulants cause an increase in blood pressure (mean increase about 2 to 4 mmHg) and heart rate (mean increase about 3 to 6 bpm). Some patients may have larger increases.

Monitor all MYDAYIS-treated patients for potential tachycardia and hypertension [see Adverse Reactions (6.1)].

5.4 Psychiatric Adverse Reactions

Exacerbation of Pre-Existing Psychosis

CNS stimulants may exacerbate symptoms of behavior disturbance and thought disorder in patients with a pre-existing psychotic disorder.

Induction of a Manic Episode in Patients with Bipolar Disorder

CNS stimulants may induce a manic or mixed episode in patients with bipolar disorder. Prior to initiating MYDAYIS treatment, screen patients for risk factors for developing a manic episode (e.g., comorbid or history of depressive symptoms or a family history of suicide, bipolar disorder, and depression).

New Psychotic or Manic Symptoms

CNS stimulants, at the recommended dosage, may cause psychotic or manic symptoms, e.g., hallucinations, delusional thinking, or mania in patients without a prior history of psychotic illness or mania. In a pooled analysis of multiple short-term, placebo-controlled studies of CNS stimulants, psychotic or manic symptoms occurred in approximately 0.1% of CNS stimulant-treated patients compared to 0% of placebo-treated patients. If such symptoms occur, consider discontinuing MYDAYIS.

5.5 Long-Term Suppression of Growth in Pediatric Patients

CNS stimulants have been associated with weight loss and slowing of growth rate in pediatric patients.

In a 4 week, placebo-controlled trial of MYDAYIS in patients ages 6 to 17 years old with ADHD, there was a decrease in weight in the MYDAYIS groups compared to weight gain in the placebo group [see Adverse Reactions (6.1)].

Closely monitor growth (weight and height) in MYDAYIS-treated pediatric patients. Pediatric patients who are not growing or gaining weight as expected may need to have their treatment interrupted. MYDAYIS is not approved for use in pediatric patients 12 years and younger [see Use in Specific Populations (8.4)].

5.6 Peripheral Vasculopathy, Including Raynaud’s Phenomenon

CNS stimulants, including MYDAYIS, used to treat ADHD are associated with peripheral vasculopathy, including Raynaud’s phenomenon. Signs and symptoms are usually intermittent and mild; however, sequelae have included digital ulceration and/or soft tissue breakdown. Effects of peripheral vasculopathy, including Raynaud’s phenomenon, were observed in post-marketing reports and at the therapeutic dosage of CNS stimulants in all age groups throughout the course of treatment. Signs and symptoms generally improved after dosage reduction or discontinuation of the CNS stimulant.

Careful observation for digital changes is necessary during MYDAYIS treatment. Further clinical evaluation (e.g., rheumatology referral) may be appropriate for MYDAYIS-treated patients who develop signs or symptoms of peripheral vasculopathy.

5.7 Seizures

MYDAYIS may lower the convulsive threshold in patients with prior history of seizure, in patients with prior EEG abnormalities in the absence of seizures, and in patients without a history of seizures and no prior EEG evidence of seizures. In the presence of seizures, MYDAYIS should be discontinued.

5.8 Serotonin Syndrome

Serotonin syndrome, a potentially life-threatening reaction, may occur when amphetamines are used in combination with other drugs that affect the serotonergic neurotransmitter systems such as monoamine oxidase inhibitors (MAOIs), selective serotonin reuptake inhibitors (SSRIs), serotonin norepinephrine reuptake inhibitors (SNRIs), triptans, tricyclic antidepressants, fentanyl, lithium, tramadol, tryptophan, buspirone, and St. John's Wort [see Drug Interactions (7.1)]. The coadministration with cytochrome P450 2D6 (CYP2D6) inhibitors may also increase the risk with increased exposure to MYDAYIS. In these situations, consider an alternative nonserotonergic drug or an alternative drug that does not inhibit CYP2D6 [see Drug Interactions (7.1)].

Serotonin syndrome symptoms may include mental status changes (e.g., agitation, hallucinations, delirium, and coma), autonomic instability (e.g., tachycardia, labile blood pressure, dizziness, diaphoresis, flushing, hyperthermia), neuromuscular symptoms (e.g., tremor, rigidity, myoclonus, hyperreflexia, incoordination), seizures, and/or gastrointestinal symptoms (e.g., nausea, vomiting, diarrhea).

Concomitant use of MYDAYIS with MAOI drugs is contraindicated [see Contraindications (4)].

Discontinue treatment with MYDAYIS and any concomitant serotonergic agents immediately if the above symptoms occur, and initiate supportive symptomatic treatment. If concomitant use of MYDAYIS with other serotonergic drugs or CYP2D6 inhibitors is clinically warranted, initiate MYDAYIS with lower doses, monitor patients for the emergence of serotonin syndrome during drug initiation or titration, and inform patients of the increased risk for serotonin syndrome.

5.9 Potential for Overdose Due to Medication Errors

Medication errors, including substitution and dispensing errors, between MYDAYIS and other amphetamine products could occur, leading to possible overdosage. To avoid substitution errors and overdosage, do not substitute for other amphetamine products on a milligram-per-milligram basis because of different amphetamine base compositions and differing pharmacokinetic profiles [see Dosage and Administration (2.7), Overdosage (10)].

5.10 Motor and Verbal Tics, and Worsening of Tourette’s Syndrome

CNS stimulants, including amphetamine, have been associated with the onset or exacerbation of motor and verbal tics. Worsening of Tourette’s syndrome has also been reported [see Adverse Reactions (6.2)].

Before initiating MYDAYIS, assess the family history and clinically evaluate patients for tics or Tourette’s syndrome. Regularly monitor MYDAYIS-treated patients for the emergence or worsening of tics or Tourette’s syndrome, and discontinue treatment if clinically appropriate.

6 ADVERSE REACTIONS

The following adverse reactions are discussed in greater detail in other sections of the labeling:

- Abuse, Misuse, and Addiction [see Boxed Warning, Warnings and Precautions (5.1), Drug Abuse and Dependence (9.2, 9.3)]
- Hypersensitivity to amphetamine products or other ingredients of MYDAYIS [see Contraindications (4)]
- Hypertensive Crisis When Used Concomitantly with Monoamine Oxidase Inhibitors [see Contraindications (4), Drug Interactions (7.1)]
- Risks to Patients with Serious Cardiac Disease [see Warnings and Precautions (5.2)]
- Increased Blood Pressure and Heart Rate [see Warnings and Precautions (5.3)]
- Psychiatric Adverse Reactions [see Warnings and Precautions (5.4)]
- Long-Term Suppression of Growth in Pediatric Patients [see Warnings and Precautions (5.5)]
- Peripheral Vasculopathy, Including Raynaud's Phenomenon [see Warnings and Precautions (5.6)]
- Seizures [see Warnings and Precautions (5.7)]
- Serotonin Syndrome [see Warnings and Precautions (5.8)]
- Motor and Verbal Tics, and Worsening of Tourette's Syndrome [see Warnings and Precautions (5.10)]

6.1 Clinical Trials Experience

Because clinical trials are conducted under widely varying conditions, adverse reaction rates observed in the clinical trials of a drug cannot be directly compared to rates in the clinical trials of another drug and may not reflect the rates observed in clinical practice.

MYDAYIS was studied in adults (18 to 55 years) and pediatric patients (13 to 17 years) who met Diagnostic and Statistical Manual of Mental Disorders, 4th or 5th editions (DSM-IV-TR® or DSM-5) criteria for ADHD. The safety data for adults were pooled from three randomized, double-blind, placebo-controlled studies in doses of 12.5 mg to 75 mg per day (1.5 times the maximum recommended dosage). Doses higher than 50 mg per day did not demonstrate additional clinical benefit and are not recommended.

The safety data for pediatric patients (13 to 17 years) is from 1 randomized, double-blind, placebo-controlled study of doses of 12.5 mg to 25 mg. The total exposure in patients treated with MYDAYIS totalled 704; this included pediatric patients, 78 adolescent patients and 626 adult patients from multiple well-controlled trials. The duration of use ranged from 4 to 7 weeks [see Clinical Studies (14)].

Adverse Reactions Leading to Discontinuation of Treatment

In pooled controlled trials of adult patients, 9% (54/626) of MYDAYIS-treated patients discontinued due to adverse reactions compared to 2% (7/328) of placebo-treated patients. The most frequent adverse reactions leading to discontinuation (i.e., leading to discontinuation in at least 1% of MYDAYIS-treated patients and at a rate at least twice that of placebo) were insomnia (2%, n=15), blood pressure increased (2%, n=10), decreased appetite (1%, n=5), and headache (1%, n=4).

In a controlled trial including adolescent patients (13 to 17 years), 5% (4/78) of MYDAYIS-treated patients discontinued due to adverse reactions compared to 0% (0/79) of placebo-treated patients. The most frequent adverse reaction leading to discontinuation (i.e., leading to discontinuation in at least 1% of MYDAYIS-treated patients and at a rate at least twice that of placebo) were dizziness (1%, n=1), depression (1%, n=1), abdominal pain upper (1%, n=1), and viral infection (1%, n=1).

Adverse Reactions Occurring at an Incidence of ≥2% and at Least Twice Placebo Among MYDAYIS-Treated Adults in Clinical Trials

The most common adverse reactions reported in adults were insomnia, decreased appetite, dry mouth, decreased weight, heart rate increased, and anxiety. Table 1 lists the adverse reactions that occurred ≥2% compared to placebo. The most common adverse reaction (insomnia) generally occurred early during treatment with MYDAYIS.

Table 1: Adverse Reactions Reported by 2% or More of Adults Taking MYDAYIS and at Least Twice the Incidence in Patients Taking Placebo in 3 Clinical Trials (4, 6, and 7 Weeks)
Body System | Adverse Reaction | MYDAYIS [Includes doses up to 75 mg (1.5 times the maximum recommended dosage).] (N = 626) | Placebo (N = 328)
Nervous System
 | Anxiety | 7% | 3%
 | Feeling Jittery | 2% | 1%
 | Agitation | 2% | 0%
 | Bruxism | 2% | 0%
Psychiatric Disorders
 | Insomnia | 31% | 8%
 | Depression | 3% | 0%
Metabolism and Nutritional Disorders
 | Decreased Appetite | 30% | 4%
 | Weight Decreased | 9% | 0%
Gastrointestinal System
 | Dry Mouth | 23% | 4%
 | Diarrhea | 3% | 1%
Cardiovascular System
 | Heart Rate Increased | 9% | 0%
 | Palpitations | 4% | 2%
Genitourinary System
 | Dysmenorrhea [Dysmenorrhea was observed in 11 females.] | 4% | 2%
 | Erectile Dysfunction [Erectile dysfunction was observed in 6 males.] | 2% | 1%

Adverse Reactions Occurring at an Incidence of 2% or More and at Least Twice Placebo Among MYDAYIS-Treated Adolescents (13 to 17 years) in a 4 Week Clinical Trial

The most common adverse reactions reported in adolescents were decreased appetite, nausea, insomnia, abdominal pain upper, irritability, and weight decreased. Table 2 lists the adverse reactions that occurred ≥2% compared to placebo.

Table 2: Adverse Reactions Reported by ≥2% or More of Adolescents Taking MYDAYIS and at Least Twice the Incidence in Patients Taking Placebo in a 4 Week Clinical Trial
Body System | Adverse Reaction | MYDAYIS (N = 78) | Placebo (N = 79)
Nervous System
 | Dizziness | 4% | 0%
Metabolism and Nutrition Disorders
 | Decreased appetite | 22% | 6%
 | Weight decreased | 5% | 1%
Psychiatric Disorders
 | Irritability | 6% | 3%
 | Insomnia [Insomnia includes terms: initial insomnia, middle insomnia, terminal insomnia and insomnia.] | 8% | 3%
Gastrointestinal Disorders
 | Nausea | 8% | 4%
 | Abdominal pain upper | 4% | 1%

6.2 Adverse Reactions Associated with the Use of Amphetamines

The following adverse reactions have been associated with the use of amphetamines. The following adverse reactions have been identified during postapproval use of amphetamines. Because these reactions are reported voluntarily from a population of uncertain size, it is not possible to reliably estimate their frequency or establish a causal relationship to drug exposure.

Allergic: Urticaria, rash, hypersensitivity reactions, including angioedema and anaphylaxis. Serious skin rashes, including Stevens-Johnson syndrome and toxic epidermal necrolysis have been reported.

Cardiovascular: Dyspnea, sudden death. There have been isolated reports of cardiomyopathy associated with chronic amphetamine use.

Central Nervous System: Psychotic episodes at recommended doses, overstimulation, restlessness, euphoria, dyskinesia, dysphoria, headache, tics, fatigue, aggression, anger, logorrhea, dermatillomania, and paresthesia (including formication), motor and verbal tics.

Endocrine: Impotence, changes in libido, frequent or prolonged erections.

Eye Disorders: Mydriasis.

Gastrointestinal: Unpleasant taste, constipation, intestinal ischemia.

Musculoskeletal and Connective Tissue Disorders: Rhabdomyolysis.

Skin: Alopecia.

Vascular Disorders: Raynaud’s phenomenon.

7 DRUG INTERACTIONS

7.1 Drugs Having Clinically Important Interactions with Amphetamines

Table 3: Drugs Having Clinically Important Interactions with Amphetamines
Monoamine Oxidase Inhibitors (MAOIs)
Clinical Impact | MAOI antidepressants slow amphetamine metabolism, increasing amphetamines effect on the release of norepinephrine and other monoamines from adrenergic nerve endings causing headaches and other signs of hypertensive crisis. Toxic neurological effects and malignant hyperpyrexia can occur, sometimes with fatal results.
Intervention | Do not administer MYDAYIS during or within 14 days following the administration of MAOI [see Contraindications (4)].
Serotonergic Drugs
Clinical Impact | The concomitant use of amphetamines and serotonergic drugs increases the risk of serotonin syndrome.
Intervention | Initiate with lower doses and monitor patients for signs and symptoms of serotonin syndrome, particularly during MYDAYIS initiation or dosage increase. If serotonin syndrome occurs, discontinue MYDAYIS and concomitant serotonergic drug(s) [see Warnings and Precautions (5.7)].
Alkalinizing Agents
Clinical Impact | May increase exposure to amphetamine and exacerbate the action of amphetamine.
Intervention | Caution should be taken when coadministering MYDAYIS and gastrointestinal and urinary alkalinizing agents.
Acidifying Agents
Clinical Impact | Lower blood levels and efficacy of amphetamines.
Intervention | Increase dose of MYDAYIS based on clinical response.
Tricyclic Antidepressants
Clinical Impact | May enhance the activity of tricyclic or sympathomimetic agents causing sustained increases in the concentration of d-amphetamine in the brain; cardiovascular effects can be potentiated.
Intervention | Monitor frequently and adjust MYDAYIS dose or use alternative therapy based on clinical response.
CYP2D6 Inhibitors
Clinical Impact | May increase the exposure of amphetamine.
Intervention | Start with lower doses and monitor frequently and adjust MYDAYIS dose or use alternative therapy based on clinical response.
Gastric pH Modulators
Clinical Impact | Potential change in shape of PK profile and exposure may occur.
Intervention | Monitor patients for changes in clinical effect and use alternative therapy based on clinical response.

7.2 Drug/Laboratory Test Interactions

Amphetamines can cause a significant elevation in plasma corticosteroid levels. This increase is greatest in the evening. Amphetamines may interfere with urinary steroid determinations.

8 USE IN SPECIFIC POPULATIONS

8.1 Pregnancy

Pregnancy Exposure Registry

There is a pregnancy exposure registry that monitors pregnancy outcomes in women exposed to MYDAYIS during pregnancy. Healthcare providers are encouraged to register patients by calling the National Pregnancy Registry for Psychiatric Medications at 1-866-961-2388 or visiting online at https://womensmentalhealth.org/research/pregnancyregistry/.

Risk Summary

The limited available data from published literature and postmarketing reports on use of amphetamine in pregnant women are not sufficient to inform a drug-associated risk for major birth defects and miscarriage. Adverse pregnancy outcomes, including premature delivery and low birth weight, have been seen in infants born to mothers dependent on amphetamines [see Clinical Considerations].

In an embryofetal development study, amphetamine (d- to l- enantiomer ratio of 3:1, the same as in MYDAYIS) had no effects on embryofetal morphological development or survival when administered to pregnant rats and rabbits throughout the period of organogenesis up to doses 10 times the maximum recommended human dose (MRHD) of 25 mg/day given to adolescents, on a mg/m^2 body surface area basis. However, in a pre- and postnatal development study, amphetamine (d- to l- ratio of 3:1) administered orally to pregnant rats during gestation and lactation caused a decrease in pup survival and a decrease in pup body weight that correlated with a delay in developmental landmarks at clinically relevant doses of amphetamine. In addition, adverse effects on reproductive performance were observed in pups whose mothers were treated with amphetamine. Long-term neurochemical and behavioral effects have also been reported in animal developmental studies using clinically relevant doses of amphetamine [see Data].

The estimated background risk of major birth defects and miscarriage for the indicated population is unknown. All pregnancies have a background risk of birth defect, loss or other adverse outcomes. In the U.S. general population, the estimated background risk of major birth defects and miscarriage in clinically recognized pregnancies is 2 to 4% and 15 to 20%, respectively.

Clinical Considerations

Fetal/Neonatal Adverse Reactions

Amphetamines, such as MYDAYIS, cause vasoconstriction and thereby may decrease placental perfusion. In addition, amphetamines can stimulate uterine contractions increasing the risk of premature delivery. Infants born to amphetamine-dependent mothers have an increased risk of premature delivery and low birth weight.

Monitor infants born to mothers taking amphetamines for symptoms of withdrawal such as feeding difficulties, irritability, agitation, and excessive drowsiness.

Data

Animal Data

Amphetamine (d- to l- enantiomer ratio of 3:1, the same as in MYDAYIS) had no apparent effects on embryofetal morphological development or survival when administered orally to pregnant rats and rabbits throughout the period of organogenesis at doses of up to 6 and 16 mg/kg/day, respectively. These doses are approximately 2 and 10 times, respectively, the maximum recommended human dose (MRHD) of 25 mg/day given to adolescents, on a mg/m^2 body surface area basis. Fetal malformations and death have been reported in mice following parenteral administration of d-amphetamine doses of 50 mg/kg/day (approximately 8 times the MRHD given to adolescents on a mg/m^2 basis) or greater to pregnant animals. Administration of these doses was also associated with severe maternal toxicity.

A pre- and postnatal development study was conducted with amphetamine (d- to l- enantiomer ratio of 3:1) in which pregnant rats received daily oral doses of 2, 6, and 10 mg/kg from gestation Day 6 to lactation Day 20. These doses are approximately 0.6, 2, and 3 times the MRHD of 25 mg/day amphetamine (d- to l- ratio of 3:1) given to adolescents, on a mg/m^2 basis. All doses caused hyperactivity and decreased weight gain in the dams. A decrease in pup survival was seen at all doses. A decrease in pup body weight was seen at 6 and 10 mg/kg which correlated with delays in developmental landmarks, such as preputial separation and vaginal opening. Increased pup locomotor activity was seen at 10 mg/kg on Day 22 postpartum but not at 5 weeks postweaning. When pups were tested for reproductive performance at maturation, gestational weight gain, number of implantations, and number of delivered pups were decreased in the group whose mothers had been given 10 mg/kg.

A number of studies from the literature in rodents indicate that prenatal or early postnatal exposure to amphetamine (d- or d, l-) at doses similar to those used clinically can result in long-term neurochemical and behavioral alterations. Reported behavioral effects include learning and memory deficits, altered locomotor activity, and changes in sexual function.

8.2 Lactation

Risk Summary

Based on limited case reports in published literature, amphetamine (d- or d, l-) is present in human milk, at relative infant doses of 2 to 13.8% of the maternal weight-adjusted dosage and a milk/plasma ratio ranging between 1.9 and 7.5. There are no reports of adverse effects on the breastfed infant. Long-term neurodevelopmental effects on infants from amphetamine exposure are unknown. It is possible that large dosages of dextroamphetamine might interfere with milk production, especially in women whose lactation is not well established. Because of the potential for serious adverse reactions in nursing infants, including serious cardiovascular reactions, blood pressure and heart rate increase, suppression of growth, and peripheral vasculopathy, advise patients that breastfeeding is not recommended during treatment with MYDAYIS.

8.4 Pediatric Use

The safety and effectiveness of MYDAYIS in pediatric patients with ADHD ages 13 to 17 years have been established in two placebo-controlled clinical studies [see Adverse Reactions (6.1), Clinical Pharmacology (12.3), Clinical Studies (14)].

The safety and effectiveness of MYDAYIS have not been established in pediatric patients ages 12 years and younger.

MYDAYIS has been studied for the treatment of ADHD in pediatric patients 6 to 12 years in two placebo controlled safety and efficacy trials. In the first trial, pediatric patients 6 to 12 years experienced higher rates of adverse reactions in some cases compared to patients 13 years and older, including higher rates of insomnia (30% vs 8%) and appetite decreased (43% vs 22%). In addition, amphetamine systemic exposures (both d- and l-) in pediatric patients 6 to 12 years following a single dose were higher than those observed in adults at the same dose (72 to 79% higher Cmax and approximately 83% higher AUC). A second trial evaluated a lower dose than those approved for pediatric patients 13 to 17 years; efficacy was not demonstrated for the lower dose. Therefore, a safe and effective dose cannot be established in pediatric patients 12 years and younger.

Growth Suppression

Growth should be monitored during treatment with stimulants, including MYDAYIS, in pediatric patients 13 to 17 years who are not growing or gaining weight as expected may need to have their treatment interrupted [see Warnings and Precautions (5.5), Adverse Reactions (6.1)].

Juvenile Animal Toxicity Data

Juvenile rats treated with mixed amphetamine salts (same as in MYDAYIS) early in the postnatal period through sexual maturation demonstrated transient changes in motor activity. Learning and memory was impaired at approximately 8 times the maximum recommended human dose (MRHD) given to children on a mg/m^2 basis. No recovery was seen following a drug-free period. A delay in sexual maturation was observed at a dose approximately 8 times the MRHD given to children on a mg/m^2 basis, although there was no effect on fertility.

In a juvenile developmental study, rats received daily oral doses of amphetamine (d to l enantiomer ratio of 3:1, the same as in MYDAYIS) of 2, 6, or 20 mg/kg on days 7 to 13 of age; from Day 14 to approximately Day 60 of age these doses were given b.i.d. for total daily doses of 4, 12, or 40 mg/kg. The latter doses are approximately 0.8, 2, and 8 times the MRHD of 25 mg/day given to children on a mg/m^2 basis. Postdosing hyperactivity was seen at all doses; motor activity measured prior to the daily dose was decreased during the dosing period but the decreased motor activity was largely absent after an 18 day drug-free recovery period. Performance in the Morris water maze test for learning and memory was impaired at the 40 mg/kg dose, and sporadically at the lower doses, when measured prior to the daily dose during the treatment period; no recovery was seen after a 19 day drug-free period. A delay in the developmental milestones of vaginal opening and preputial separation was seen at 40 mg/kg but there was no effect on fertility.

8.5 Geriatric Use

Clinical studies of MYDAYIS did not include sufficient numbers of subjects aged 65 and over to determine whether they respond differently from younger subjects. Other reported clinical experience has not identified differences in responses between the elderly and younger patients. In general, dose selection for an elderly patient should start at the low end of the dosing range, reflecting the greater frequency of decreased hepatic, renal, or cardiac function, and of concomitant disease or other drug therapy.

8.6 Renal Impairment

Due to reduced clearance of amphetamine in patients with severe renal insufficiency (GFR 15 to <30 mL/min/1.73 m^2), the maximum dose in adults should be reduced. Pediatric patients ages 13 to 17 years with severe renal insufficiency can be given the recommended starting dose if tolerated, but the dose should not be escalated. MYDAYIS is not recommended in patients with ESRD (GFR <15 mL/min/1.73 m^2) [see Dosage and Administration (2.6), Clinical Pharmacology (12.3)].

d-Amphetamine is not dialyzable.

9 DRUG ABUSE AND DEPENDENCE

9.1 Controlled Substance

MYDAYIS contains mixed amphetamine salts, a Schedule II controlled substance.

9.2 Abuse

MYDAYIS has a high potential for abuse and misuse which can lead to the development of a substance use disorder, including addiction [see Warnings and Precautions (5.1)]. MYDAYIS can be diverted for non-medical use into illicit channels or distribution.

Abuse is the intentional non-therapeutic use of a drug, even once, to achieve a desired psychological or physiological effect. Misuse is the intentional use, for therapeutic purposes, of a drug by an individual in a way other than prescribed by a healthcare provider or for whom it was not prescribed. Drug addiction is a cluster of behavioral, cognitive, and physiological phenomena that may include a strong desire to take the drug, difficulties in controlling drug use (e.g., continuing drug use despite harmful consequences, giving a higher priority to drug use than other activities and obligations), and possible tolerance or physical dependence.

Misuse and abuse of amphetamine may cause increased heart rate, respiratory rate, or blood pressure; sweating; dilated pupils; hyperactivity; restlessness; insomnia; decreased appetite; loss of coordination; tremors; flushed skin; vomiting; and/or abdominal pain. Anxiety, psychosis, hostility, aggression, and suicidal or homicidal ideation have also been observed with CNS stimulants abuse and/or misuse. Misuse and abuse of CNS stimulants, including MYDAYIS, can result in overdose and death [see Overdosage (10)], and this risk is increased with higher doses or unapproved methods of administration, such as snorting or injection.

9.3 Dependence

Physical Dependence

MYDAYIS may produce physical dependence. Physical dependence is a state that develops as a result of physiological adaptation in response to repeated drug use, manifested by withdrawal signs and symptoms after abrupt discontinuation or a significant dose reduction of a drug.

Withdrawal signs and symptoms after abrupt discontinuation or dose reduction following prolonged use of CNS stimulants including MYDAYIS include dysphoric mood; depression; fatigue; vivid, unpleasant dreams; insomnia or hypersomnia; increased appetite; and psychomotor retardation or agitation.

Tolerance

MYDAYIS may produce tolerance. Tolerance is a physiological state characterized by a reduced response to a drug after repeated administration (i.e., a higher dose of a drug is required to produce the same effect that was once obtained at a lower dose).

10 OVERDOSAGE

Clinical Effects of Overdose

Overdose of CNS stimulants is characterized by the following sympathomimetic effects:

- Cardiovascular effects including tachyarrhythmias, and hypertension or hypotension. Vasospasm, myocardial infarction, or aortic dissection may precipitate sudden cardiac death. Takotsubo cardiomyopathy may develop.
- CNS effects including psychomotor agitation, confusion, and hallucinations. Serotonin syndrome, seizures, cerebral vascular accidents, and coma may occur.
- Life-threatening hyperthermia (temperatures greater than 104°F) and rhabdomyolysis may develop.

Overdose Management

Consider the possibility of multiple drug ingestion. The pharmacokinetic profile of MYDAYIS should be considered when treating patients with overdose. D-amphetamine is not dialyzable. Consider contacting the Poison Help line (1-800-222-1222) or a medical toxicologist for additional overdose management recommendations.

11 DESCRIPTION

MYDAYIS extended-release capsules contain mixed salts of a single-entity amphetamine, a CNS stimulant. MYDAYIS contains equal amounts (by weight) of four salts: dextroamphetamine sulfate and amphetamine sulfate, dextroamphetamine saccharate and amphetamine aspartate monohydrate. This results in a 3:1 mixture of dextro- to levo- amphetamine base equivalent.

The 12.5 mg, 25 mg, 37.5 mg, and 50 mg strength capsules are for oral administration. They contain three types of drug-releasing beads, an immediate release and two different types of delayed release (DR) beads. The first DR bead releases amphetamine at pH 5.5 and the other DR bead releases amphetamine at pH 7.0.

 | CAPSULE STRENGTHS
EACH CAPSULE CONTAINS: | 12.5 mg | 25 mg | 37.5 mg | 50 mg
Dextroamphetamine Saccharate | 3.125 mg | 6.250 mg | 9.375 mg | 12.500 mg
Amphetamine Aspartate Monohydrate | 3.125 mg | 6.250 mg | 9.375 mg | 12.500 mg
Dextroamphetamine Sulfate | 3.125 mg | 6.250 mg | 9.375 mg | 12.500 mg
Amphetamine Sulfate | 3.125 mg | 6.250 mg | 9.375 mg | 12.500 mg
Total mixed amphetamine salts | 12.500 mg | 25 mg | 37.5 mg | 50 mg
Total amphetamine base equivalence | 7.8 mg | 15.6 mg | 23.5 mg | 31.3 mg

Inactive Ingredients and Colors

The inactive ingredients in MYDAYIS capsules include: hard gelatin capsules, ethylcellulose, hydroxypropyl methylcellulose, methacrylic acid copolymer, methyl acrylate, methyl methacrylate, methacrylic acid copolymer, Opadry® beige, sugar spheres, talc, and triethyl citrate. The gelatin capsules for all four strengths contain gelatin, titanium dioxide, yellow iron oxide, and edible inks. The 12.5 mg and 25 mg strength gelatin capsules also contain FD&C Blue #2. The 37.5 mg strength also contains red iron oxide. The 50 mg strength capsule also contains D&C Red #28, D&C Red #33, and FD&C Blue #1.

12 CLINICAL PHARMACOLOGY

12.1 Mechanism of Action

Amphetamines are non-catecholamine sympathomimetic amines with CNS stimulant activity. The exact mode of therapeutic action in ADHD is not known.

12.2 Pharmacodynamics

Amphetamines block the reuptake of norepinephrine and dopamine into the presynaptic neuron and increase the release of these monoamines into the extraneuronal space.

12.3 Pharmacokinetics

MYDAYIS contains d-amphetamine and l-amphetamine salts in the ratio of 3:1. Pharmacokinetic studies of d- and l-amphetamine after oral administration of MYDAYIS have been conducted in healthy adults (19 to 52 years) and pediatric patients (6 to 17 years) with ADHD. Following administration of MYDAYIS, the peak plasma concentrations occurred in about 7 to 10 hours in pediatric patients and about 8 hours in adults for both d-amphetamine and l-amphetamine. The mean plasma elimination half-life for d-amphetamine ranges from about 10 to 11 hours and l-amphetamine from 10 to 13 hours in both pediatric and adult patients.

Absorption

MYDAYIS exhibits linear dose proportionality over the range of 12.5 to 50 mg. Steady-state is achieved between Days 7 and 8 of dosing with mean accumulation ratio of 1.6. A single dose of MYDAYIS 37.5 mg capsules provided comparable plasma concentration profiles of both d- and l-amphetamine to mixed amphetamine salts extended release (MAS-ER) 25 mg followed by 12.5 mg immediate release amphetamine administered 8 hours later (Figure 1).

Figure 1: Mean Plasma Concentrations of d- and l-amphetamine Following Oral Administration of MYDAYIS 37.5 mg vs MAS-ER 25 mg Followed by Immediate-Release MAS-IR 12.5 mg 8 Hours Later in Adults

Effect of Food

High fat meal does not affect the extent of absorption of d- and l-amphetamine when taken with MYDAYIS. Tmax is prolonged by 5 hours (from 7.0 hours at fasted state to 12.0 hours after a high-fat meal) for d-amphetamine and 4.5 hours (from 7.5 hours at fasted state to 12 hours after a high-fat meal) for l-amphetamine after administration of MYDAYIS 50 mg with high fat meal. Opening the capsule and sprinkling the contents on applesauce results in comparable absorption and exposure to the intact capsule taken in the fasted state [see Dosage and Administration (2.3)].

Effect of Alcohol

The in vitro testing showed increases in amphetamine release rate from MYDAYIS capsules in the presence of 20% and, more noticeably, 40% alcohol. There is no in vivo study conducted for the effect of alcohol on drug exposure.

Elimination

Metabolism

Amphetamine is reported to be oxidized at the 4 position of the benzene ring to form 4-hydroxyamphetamine, or on the side chain α or β carbons to form alpha-hydroxy-amphetamine or norephedrine, respectively. Norephedrine and 4-hydroxy-amphetamine are both active and each is subsequently oxidized to form 4-hydroxy-norephedrine. Alpha-hydroxy-amphetamine undergoes deamination to form phenylacetone, which ultimately forms benzoic acid and its glucuronide and the glycine conjugate hippuric acid. Although the enzymes involved in amphetamine metabolism have not yet been clearly defined, CYP2D6 is known to be involved with formation of 4-hydroxy-aphetamine. Since CYP2D6 is genetically polymorphic, population variations in amphetamine metabolism are a possibility.

Amphetamine is known to inhibit monoamine oxidase. Amphetamines are not an in vitro inhibitor of the major human CYP450 isoforms (CYP1A2, CYP2C9, CYP2C19, CYP2D6, and CYP3A4), nor was it an in vitro inducer of CYP1A2, CYP2B6 or CYP3A4/5. Amphetamines are not an in vitro substrate for P-gp.

Excretion

The renal excretion is the primary route for elimination of d- and l-amphetamine and its metabolites after administration of MYDAYIS.

At normal urine pHs, approximately half of an administered dose of amphetamine is recoverable in urine as derivatives of alpha-hydroxy-amphetamine and approximately another 30 to 40% of the dose is recoverable in urine as amphetamine itself. Urinary recovery of amphetamine is highly dependent on pH and urine flow rates. Alkaline urine pHs result in less ionization and reduced renal elimination, and acidic pHs and high flow rates result in increased renal elimination. Urinary recovery of amphetamine has been reported to range from 1% to 75%, and the fraction of a dose hepatically metabolized is dependent on urine pH. Consequently, both hepatic and renal dysfunctions have the potential to alter the elimination of amphetamine and could result in prolonged exposures [see Drug Interactions (7.1)].

Specific Populations

Age

Comparison of the pharmacokinetics of d- and l-amphetamine after oral administration of MYDAYIS in pediatric patients with ADHD 13 to 17 years old and healthy adult subjects (19 to 52 years) indicates that body weight is the primary determinant of apparent differences in the pharmacokinetics of d- and l-amphetamine across the age range.

PK data from patients age 13 to 17 years (n=14) who received a single 25 mg MYDAYIS capsule was scaled (based on PK proportionality) and compared with PK data from adult patients 19 to 51 years (n=20) who received 37.5 mg. Based on dose proportionality, a single-dose MYDAYIS capsule administered to pediatric patients age 13 to 17 years (n=14) would produce about 21% to 31% higher Cmax for d- and l-amphetamine and 21% to 31% higher AUC for d- and l-amphetamine, compared to the same dose of MYDAYIS capsule administered to adults (age 19 to 51 years).

Male and Female Patients

In pharmacokinetic studies, systemic exposure to d- and l-amphetamine was similar in women (N=41) and in men (N=61).

Racial Groups

Formal pharmacokinetic studies for race have not been conducted. However, amphetamine pharmacokinetics appeared to be comparable among Whites (N=41), Blacks (N=27), and Hispanics (N=34).

Patients with Renal impairment

The effect of renal impairment on d- and l-amphetamine after administration of MYDAYIS has not been studied.

In a pharmacokinetic study of lisdexamfetamine in adult subjects with normal and impaired renal function mean d-amphetamine clearance was reduced from 0.7 L/hr/kg in normal subjects to 0.4 L/hr/kg in subjects with severe renal impairment (GFR 15 to <30 mL/min/1.73 m^2) patients. Dialysis did not significantly affect the clearance of d-amphetamine. The impact of renal impairment on the disposition of amphetamine would be expected to be similar between oral administration of lisdexamfetamine and MYDAYIS [see Use in Specific Populations (8.6)].

13 NONCLINICAL TOXICOLOGY

13.1 Carcinogenesis, Mutagenesis, Impairment of Fertility

Carcinogenesis

No evidence of carcinogenicity was found in studies in which d, l-amphetamine (enantiomer ratio of 1:1) was administered to mice and rats in the diet for 2 years at doses of up to 30 mg/kg/day in male mice, 19 mg/kg/day in female mice, and 5 mg/kg/day in male and female rats. These doses are approximately 3, 2, and 1 times, respectively, the maximum recommended human dose of 50 mg/day on a mg/m^2 body surface area basis in adults.

Mutagenesis

Amphetamine, in the enantiomer ratio present, d- to l- ratio of 3:1, was not clastogenic in the mouse bone marrow micronucleus test in vivo and was negative when tested in the E. coli component of the Ames test in vitro. d, l-Amphetamine (1:1 enantiomer ratio) has been reported to produce a positive response in the mouse bone marrow micronucleus test, an equivocal response in the Ames test, and negative responses in the in vitro sister chromatid exchange and chromosomal aberration assays.

Impairment of Fertility

Amphetamines, in the enantiomer ratio, d- to l- ratio of 3:1, did not adversely affect fertility or early embryonic development in the rat at doses of up to 20 mg/kg/day (approximately 6 times the maximum recommended human dose of 25 mg/day given to adolescents on a mg/m^2 body surface area basis).

13.2 Animal Toxicology and/or Pharmacology

Acute administration of high doses of amphetamine (d- or d, l-) has been shown to produce long-lasting neurotoxic effects, including irreversible nerve fiber damage in rodents. The significance of these findings to humans is unknown.

14 CLINICAL STUDIES

Efficacy of MYDAYIS in the treatment of ADHD was established in the following trials:

- Three short-term trials in adults (18 to 55 years, Studies 1, 2, and 3)
- Two short-term trials in pediatric patients (13 to 17 years, Studies 4 and 5)

Adult Patients (18 to 55 years) with ADHD

The approved adult doses, 12.5 mg, 25 mg, and 37.5 mg are based on Studies 1 and 3 and the 50 mg dose efficacy is based on Study 2. Doses up to 75 mg per day (1.5 times the maximum recommended adult dosage) were evaluated, but demonstrated no additional clinical benefit.

A 4 week, randomized, double-blind, multicenter, placebo-controlled, forced-dose titration, safety and efficacy study (Study 1) was conducted in adults aged 18 to 55 years (N=275) who met DSM-5 criteria for ADHD. Patients were randomized in a 1:1:1 ratio, to two MYDAYIS treatment groups and a placebo group. Group 1 received a dose of 12.5 mg/day throughout the study. Group 2 were titrated on a weekly basis from the initial dose 12.5 mg until target dose of 37.5 mg/day was reached by Week 3 and were maintained at 37.5 mg throughout the study. Group 3 received placebo.

The primary efficacy endpoint was defined as the change from baseline of the adult ADHD-Rating Scale (RS) with prompts total score at Week 4. Baseline adult ADHD-RS with prompts total score was defined as the last valid adult ADHD-RS with prompts total score assessment prior to taking the first dose of double-blind investigational product, usually at Visit 2. The primary comparison of interest was at Week 4 for each MYDAYIS dose compared with placebo. MYDAYIS demonstrated a statistically significant treatment effect compared with placebo on change of ADHD-RS total score from baseline at visit 6 (Week 4), for both 12.5 mg and 37.5 mg doses respectively (Study 1 in Table 4). Patients on MYDAYIS also showed statistically significantly greater improvement on the Clinical Global Impression of Improvement (CGI-I) score compared with placebo treatment.

Two multicenter, randomized, double-blind, placebo-controlled, crossover studies of MYDAYIS 25 mg/day (Study 3) and 50 mg/day (Study 2) were conducted in adult patients who met DSM-IV TR criteria for ADHD. The efficacy was determined using the Permanent Product Measure of Performance (PERMP), a skill-adjusted math test that measures attention in ADHD. PERMP total score results from the sum of the number of math problems attempted plus the number of math problems answered correctly. Efficacy assessments were conducted at 2, 4, 8, 12, 14, and 16 hours post-dose using the PERMP. MYDAYIS treatment, compared to placebo, reached statistical significance at either 2 hours (Study 2) or 4 hours (Study 3) post-dose to 16 hours post-dose in both studies. In a prespecified supplementary analysis for Study 2, the maximum approved dose of MYDAYIS (50 mg) demonstrated a statistically significant treatment effect compared with placebo beginning at 2 to 16 hours post-dose (Study 2 and Study 3 in Table 4).

Pediatric Patients (13 to 17 years) with ADHD

A 4 week, randomized, double-blind, multicenter, placebo-controlled, dose-optimization, safety and efficacy study (Study 4) was conducted. In Study 4, the 157 pediatric patients 13 to 17 years old who met DSM-IV TR criteria for ADHD, were randomized in a 1:1 ratio to MYDAYIS or placebo group. Subjects were titrated from a dose of 12.5 mg/day until an optimal dose was reached (up to a maximum dose of 25 mg); this dose was maintained during the dose-maintenance period (Study 4 in Table 4).

The primary efficacy endpoint was defined as the change from baseline of the ADHD-RS-IV Total Score at Week 4. The baseline ADHD-RS-IV Total Score was defined as the last valid ADHD-RS-IV Total Score assessment prior to taking the first dose of double-blind investigational product, usually at Visit 2. MYDAYIS demonstrated a statistically significant treatment effect compared with placebo on the change of ADHD RS-IV total scores from baseline at Visit 6 (Week 4). MYDAYIS also showed statistically significantly greater improvement on the Clinical Global Impression of Improvement (CGI-I) score at Visit 6 (Week 4).

A multicenter, randomized, double-blind, placebo-controlled, crossover study of MYDAYIS 25 mg/day (Study 5) was conducted in adolescent patients who met DSM-IV TR criteria for ADHD. The efficacy was determined using the Permanent Product Measure of Performance (PERMP), a skill-adjusted math test that measures attention in ADHD. PERMP total score results from the sum of the number of math problems attempted plus the number of math problems answered correctly. Efficacy assessments were conducted at 2, 4, 8, 12, 14, and 16 hours post-dose using the PERMP. MYDAYIS treatment, compared to placebo, reached statistical significance at 2 to 16 hours post-dose (Study 5 in Table 4, Figure 2).

Figure 2: LS Mean (SE) PERMP Total Score by Treatment and Time-Point for Adolescents Ages 13 to 17 with ADHD After 1 Week of Double Blind Treatment (Study 5)

LS Mean: least-squares mean; SE: standard error

In both adults and pediatric patients, examination of a population subset based on gender or race did not reveal any differences.

Table 4: Summary of Primary Efficacy Results from Short-Term Studies of MYDAYIS in Adult and Pediatric Patients with ADHD
Study Number (Age range) | Primary Endpoint | Treatment Group | Mean Baseline Score (SD) | LS Mean Change from Baseline | Placebo-subtracted Difference [Difference (drug minus placebo) in least-squares mean change from baseline.] (95% CI)
Adult Studies
Study 1 (18 to 55 years) | ADHD-RS | MYDAYIS (12.5 mg/day) [Doses statistically significantly superior to placebo.] | 39.8 (6.38) | -18.5 | -8.1 (-11.7, -4.4)
Study 1 (18 to 55 years) | ADHD-RS | MYDAYIS (37.5 mg/day) | 39.9 (7.07) | -23.8 | -13.4 (-17.1, -9.7)
Study 1 (18 to 55 years) | ADHD-RS | Placebo | 40.5 (6.52) | -10.4
Study 2 (18 to 55 years) | Average PERMP | MYDAYIS (50 mg/day) | 239.2 (75.6) [Pre-dose PERMP total score.] | 293.23 [LS Mean for PERMP is post-dose average score over all sessions of the treatment day, rather than change from baseline.] | 18.38 (11.28, 25.47)
Study 2 (18 to 55 years) | Average PERMP | Placebo | 249.6 (76.7) | 274.85
Study 3 (18 to 55 years) | Average PERMP | MYDAYIS (25 mg/day) | 217.5 (59.6) | 267.96 | 19.29 (10.95, 27.63)
Study 3 (18 to 55 years) | Average PERMP | Placebo | 226.9 (61.7) | 248.67
Pediatric Studies
Study 4 (13 to 17 years) [Results represent subgroup of Study 4 and not the total population.] | ADHD-RS-IV | MYDAYIS (12.5-25 mg/day) | 36.7 (6.15) | -20.3 | -8.7 (-12.6, -4.8)
Study 4 (13 to 17 years) [Results represent subgroup of Study 4 and not the total population.] | ADHD-RS-IV | Placebo | 38.3 (6.67) | -11.6
Study 5 (13 to 17 years) | Average PERMP | MYDAYIS (25 mg/day) | 214.5 (87.8) | 272.67 | 41.26 (32.24, 50.29)
Study 5 (13 to 17 years) | Average PERMP | Placebo | 228.7 (101) | 231.41
SD: standard deviation; LS Mean: least-squares mean; CI: confidence interval.

16 HOW SUPPLIED/STORAGE AND HANDLING

How Supplied

MYDAYIS extended-release capsules are available as:

- 12.5 mg: Green body/green cap (imprinted with black SHIRE 465 and 12.5 mg), bottles of 100, NDC 54092-468-01
- 25 mg: Ivory body/green cap (imprinted with black SHIRE 465 and 25 mg), bottles of 100, NDC 54092-471-01
- 37.5 mg: Ivory body/caramel cap (imprinted with black SHIRE 465 and 37.5 mg), bottles of 100, NDC 54092-474-01
- 50 mg: Ivory body/purple cap (imprinted with black SHIRE 465 and 50 mg), bottles of 100, NDC 54092-477-01

Storage and Handling

Dispense in a tight, light-resistant container as defined in the USP.

Store at room temperature, 20ºC to 25ºC (68ºF to 77ºF). Excursions permitted between 15ºC to 30ºC (59ºF to 86ºF) [see USP Controlled Room Temperature].

17 PATIENT COUNSELING INFORMATION

Advise the patient to read the FDA-approved patient labeling (Medication Guide).

Abuse, Misuse, and Addiction

Educate patients and their families about the risks of abuse, misuse, and addiction of MYDAYIS, which can lead to overdose and death, and proper disposal of any unused drug [see Warnings and Precautions (5.1), Drug Abuse and Dependence (9.2), Overdosage (10)]. Advise patients to store MYDAYIS in a safe place, preferably locked, and instruct patients to not give MYDAYIS to anyone else.

Risks to Patients with Serious Cardiac Disease

Advise patients that there are potential risks to patients with serious cardiac disease, including sudden death with MYDAYIS use. Instruct patients to contact a healthcare provider immediately if they develop symptoms such as exertional chest pain, unexplained syncope, or other symptoms suggestive of cardiac disease [see Warnings and Precautions (5.2)].

Increased Blood Pressure and Heart Rate

Instruct patients that MYDAYIS can cause elevations of their blood pressure and pulse rate and they should be monitored for such effects [see Warnings and Precautions (5.3)].

Psychiatric Adverse Reactions

Advise patients that MYDAYIS, at recommended doses, may cause psychotic or manic symptoms even in patients without prior history of psychotic symptoms or mania [see Warnings and Precautions (5.4)].

Long-Term Suppression of Growth in Pediatric Patients

Advise patients, family members, and caregivers that MYDAYIS may cause slowing of growth including weight loss [see Warnings and Precautions (5.5)].

Circulation Problems in Fingers and Toes [Peripheral Vasculopathy, Including Raynaud's Phenomenon]

Instruct patients beginning treatment with MYDAYIS about the risk of peripheral vasculopathy, including Raynaud's phenomenon, and associated signs and symptoms: fingers or toes may feel numb, cool, painful, and/or may change from pale, to blue, to red. Instruct patients to report to their physician any new numbness, pain, skin color change, or sensitivity to temperature in fingers or toes. Instruct patients to call their physician immediately with any signs of unexplained wounds appearing on fingers or toes while taking MYDAYIS. Further clinical evaluation (e.g., rheumatology referral) may be appropriate for certain patients [see Warnings and Precautions (5.6)].

Seizures

Caution patient that MYDAYIS may lower the convulsive threshold. Advise patients to contact their healthcare provider immediately and to discontinue MYDAYIS if a seizure occurs [see Warnings and Precautions (5.7)].

Serotonin Syndrome

Caution patients about the risk of serotonin syndrome with concomitant use of MYDAYIS and other serotonergic drugs including SSRIs, SNRIs, triptans, tricyclic antidepressants, fentanyl, lithium, tramadol, tryptophan, buspirone, St. John's Wort, and with drugs that impair metabolism of serotonin (in particular MAOIs, both those intended to treat psychiatric disorders and also others such as linezolid [see Contraindications (4), Warnings and Precautions (5.8), Drug Interactions (7.1)]. Advise patients to contact their healthcare provider or report to the emergency room if they experience signs or symptoms of serotonin syndrome.

Motor and Verbal Tics, and Worsening of Tourette's Syndrome

Advise patients that motor and verbal tics and worsening of Tourette’s syndrome may occur during treatment with MYDAYIS. Instruct patients to notify their healthcare provider if emergence of new tics or worsening of tics or Tourette’s syndrome occurs [see Warnings and Precautions (5.10)].

Concomitant Medications

Advise patients to notify their physicians if they are taking, or plan to take, any prescription or over-the-counter drugs because there is a potential for interactions [see Drug Interactions (7.1)].

Pregnancy Registry

Advise patients that there is a pregnancy exposure registry that monitors pregnancy outcomes in women exposed to MYDAYIS during pregnancy [see Use in Specific Populations (8.1)].

Pregnancy

Advise patients of the potential fetal effects from the use of MYDAYIS during pregnancy. Advise patients to notify their healthcare provider if they become pregnant or intend to become pregnant during treatment with MYDAYIS [see Use in Specific Populations (8.1)].

Lactation

Advise women not to breastfeed if they are taking MYDAYIS [see Use in Specific Populations (8.2)].

Alcohol

Advise patients to avoid alcohol while taking MYDAYIS. Consumption of alcohol while taking MYDAYIS may result in a more rapid release of the dose of mixed amphetamine salts [see Clinical Pharmacology (12.3)].

Distributed by:
Takeda Pharmaceuticals America, Inc.
Cambridge, MA 02142

For more information call 1-877-825-3327.

MYDAYIS is a registered trademark of Takeda Pharmaceuticals U.S.A., Inc.

DSM-IV-TR is a registered trademark of the American Psychiatric Association.

OPADRY is a registered trademark of BPSI Holdings, LLC.

© 2025 Takeda Pharmaceuticals U.S.A., Inc. All rights reserved.

Patented: see www.takeda.com/en-us/patents.

MYD365

MEDICATION GUIDE
MYDAYIS® (my-DAY-is)
(mixed salts of a single-entity amphetamine product)
extended-release capsules, CII

What is the most important information I should know about MYDAYIS?
MYDAYIS may cause serious side effects, including:

- Abuse, misuse, and addiction. MYDAYIS has a high chance for abuse and misuse and may lead to substance use problems, including addiction. Misuse and abuse of MYDAYIS, other amphetamine containing medicines, and methylphenidate containing medicines, can lead to overdose and death. The risk of overdose and death is increased with higher doses of MYDAYIS or when it is used in ways that are not approved, such as snorting or injection.
  - Your healthcare provider should check you or your child’s risk for abuse, misuse, and addiction before starting treatment with MYDAYIS and will monitor you or your child during treatment.
  - MYDAYIS may lead to physical dependence after prolonged use, even if taken as directed by your healthcare provider.
  - Do not give MYDAYIS to anyone else. See “What is MYDAYIS?” for more information.
  - Keep MYDAYIS in a safe place and properly dispose of any unused medicine. See “How should I store MYDAYIS?” for more information.
    Tell your healthcare provider if you or your child have ever abused or been dependent on alcohol, prescription medicines or street drugs.
- Risks for people with serious heart disease. Sudden death has happened in people who have heart defects or other serious heart disease.
  Your healthcare provider should check you or your child carefully for heart problems before starting MYDAYIS. Tell your healthcare provider if you or your child have any heart problems, heart disease, heart defects.
  Call your healthcare provider or go to the nearest hospital emergency room right away if you or your child have any signs of heart problems such as chest pain, shortness of breath, or fainting during treatment with MYDAYIS.
- Increased blood pressure and heart rate.
  Your healthcare provider should check you or your child’s blood pressure and heart rate regularly during treatment with MYDAYIS.
- Mental (psychiatric) problems, including:
  - new or worse behavior and thought problems
  - new or worse bipolar illness
  - new psychotic symptoms (such as hearing voices, or seeing or believing things that are not real) or new manic symptoms
    Tell your healthcare provider about any mental problems you or your child have, or about a family history of suicide, bipolar illness, or depression.
    Call your healthcare provider right away if you or your child have any new or worsening mental symptoms or problems while taking MYDAYIS, especially hearing voices, seeing or believing things that are not real, or new manic symptoms.

What is MYDAYIS?
MYDAYIS is a central nervous system (CNS) stimulant prescription medicine used for the treatment of Attention Deficit Hyperactivity Disorder (ADHD) in people 13 years of age and older.
MYDAYIS is not for use in children 12 years of age and younger.
MYDAYIS is a federally controlled substance (CII) because it contains amphetamine that can be a target for people who abuse prescription medicines or street drugs. Keep MYDAYIS in a safe place to protect it from theft. Never give your MYDAYIS to anyone else, because it may cause death or harm them. Selling or giving away MYDAYIS may harm others and is against the law.

Do not take MYDAYIS if you or your child are:

- allergic to amphetamine or any of the ingredients in MYDAYIS. See the end of the Medication Guide for a complete list of ingredients in MYDAYIS.
- taking, or have taken within the past 14 days, a medicine used to treat depression called a monoamine oxidase inhibitor (MAOI).

Before taking MYDAYIS, tell your healthcare provider about all medical conditions, including if you or your child:

- have heart problems, heart disease, heart defects or high blood pressure
- have mental problems including psychosis, mania, bipolar illness or depression, or have a family history of suicide, bipolar illness, or depression
- have circulation problems in fingers and toes
- have or have had seizures
- have kidney problems
- have or had repeated movements or sounds (tics) or Tourette’s syndrome, or have a family history of tics or Tourette’s syndrome
- are pregnant or plan to become pregnant. It is not known if MYDAYIS will harm your unborn baby. Tell your healthcare provider if you become pregnant during treatment with MYDAYIS.
  - There is a pregnancy registry for females who are exposed to MYDAYIS during pregnancy. The purpose of the registry is to collect information about the health of females exposed to MYDAYIS and their baby. If you or your child becomes pregnant during treatment with MYDAYIS, talk to your healthcare provider about registering with the National Pregnancy Registry for Psychiatric Medications at 1-866-961-2388 or visit online at https://womensmentalhealth.org/research/pregnancyregistry/.
- are breastfeeding or plan to breastfeed. MYDAYIS passes into breast milk. You should not breastfeed during treatment with MYDAYIS.

Tell your healthcare provider about all the medicines that you or your child take, including prescription and over-the-counter medicines, vitamins, and herbal supplements.

MYDAYIS may affect the way other medicines work and other medicines may affect how MYDAYIS works. Taking MYDAYIS with other medicines can cause serious side effects.

Especially tell your healthcare provider if you or your child take:

- selective serotonin reuptake inhibitors (SSRIs)
- medicines used to treat migraine headaches called triptans
- lithium
- tramadol
- buspirone

- serotonin norepinephrine reuptake inhibitors (SNRIs)
- tricyclic antidepressants
- fentanyl
- tryptophan
- St. John’s Wort

Know the medicines that you or your child take. Keep a list of your medicines with you to show your or your child’s healthcare provider and pharmacist when you or your child get a new medicine.

Your healthcare provider will decide whether MYDAYIS can be taken with other medicines. Do not start any new medicine during treatment with MYDAYIS without talking to your or your child’s healthcare provider first.

How should I take MYDAYIS?

- Take MYDAYIS exactly as prescribed by your healthcare provider.
- Your healthcare provider may change the dose if needed.
- Take MYDAYIS 1 time each day in the morning right after you wake-up. MYDAYIS may last up to 16 hours and can cause difficulty sleeping.
- If you miss a dose of MYDAYIS, do not take your dose later in the day or double your dose to make up for a missed dose. Take your MYDAYIS dose the next morning at your regularly scheduled time.
- MYDAYIS can be taken with or without food but take it the same way each time.
- MYDAYIS capsules may be swallowed whole or if MYDAYIS capsules cannot be swallowed whole, the capsules may be opened and sprinkled over a spoonful of applesauce.
  - swallow all of the applesauce and medicine mixture right away
  - do not chew the applesauce and medicine mixture
  - do not store the sprinkled applesauce

If you or your child take too much MYDAYIS, call your healthcare provider or Poison Help line at 1-800-222-1222 or go to the nearest hospital emergency room right away.

What should I avoid during treatment with MYDAYIS?
You should avoid drinking alcohol during treatment with MYDAYIS.

What are possible side effects of MYDAYIS?
MYDAYIS may cause serious side effects, including:

- See "What is the most important information I should know about MYDAYIS?"
- Slowing of growth (height and weight) in children. Children should have their height and weight checked often during treatment with MYDAYIS. Your healthcare provider may stop your child's MYDAYIS treatment if they are not growing or gaining weight as expected.
- Circulation problems in fingers and toes (peripheral vasculopathy, including Raynaud's phenomenon). Signs and symptoms may include:
  - fingers or toes may feel numb, cool, painful
  - fingers or toes may change color from pale, to blue, to red
  Tell your healthcare provider if you have or your child has any numbness, pain, skin color change, or sensitivity to temperature in your fingers or toes.
  Call your healthcare provider if you or your child have any signs of unexplained wounds appearing on fingers or toes during treatment with MYDAYIS.

- Seizures. Your healthcare provider will stop treatment with MYDAYIS if you have a seizure.
- New or worsening tics or worsening Tourette's Syndrome. Tell your healthcare provider if you or your child get any new or worsening tics or worsening Tourette’s syndrome during treatment with MYDAYIS.
- Serotonin syndrome. This problem may happen when MYDAYIS is taken with certain other medicines and may be life-threatening. Call your healthcare provider or go to the nearest hospital emergency room if you get symptoms of serotonin syndrome which may include:

- agitation, hallucinations, coma
- loss of coordination
- flushing
- fast heartbeat
- seizures
- confusion

- sweating or fever
- nausea, vomiting, or diarrhea
- dizziness
- changes in blood pressure
- muscle stiffness or tightness
- high body temperature (hyperthermia)

The most common side effects of MYDAYIS include:

- trouble sleeping
- decreased appetite
- dry mouth

- increased heart rate
- anxiety
- nausea

- irritability
- weight loss

These are not all the possible side effects of MYDAYIS.

Call your doctor for medical advice about side effects. You may report side effects to FDA at 1-800-FDA-1088.

How should I store MYDAYIS?

- Store MYDAYIS at room temperature between 68°F to 77°F (20°C to 25°C).
- Protect MYDAYIS from light.
- Store MYDAYIS in a safe place, like a locked cabinet.
- Dispose of remaining, unused, or expired MYDAYIS by a medicine take-back program at a U.S. Drug Enforcement Administration (DEA) authorized collection site. If no take-back program or DEA authorized collector is available, mix MYDAYIS with an undesirable, nontoxic substance such as dirt, cat litter, or used coffee grounds to make it less appealing to children and pets. Place the mixture in a container such as a sealed plastic bag and throw away MYDAYIS in the household trash. Visit www.fda.gov/drugdisposal for additional information on disposal of unused medicines.

Keep MYDAYIS and all medicines out of the reach of children.

General information about the safe and effective use of MYDAYIS

Medicines are sometimes prescribed for purposes other than those listed in a Medication Guide. Do not use MYDAYIS for a condition for which it was not prescribed. Do not give MYDAYIS to other people, even if they have the same condition. It may harm them and it is against the law. You can ask your healthcare provider or pharmacist for information about MYDAYIS that is written for healthcare professionals.

What are the ingredients in MYDAYIS?

Active ingredients: dextroamphetamine sulfate and amphetamine sulfate, dextroamphetamine saccharate and amphetamine aspartate monohydrate

Inactive ingredients: hard gelatin capsules, ethylcellulose, hydroxypropyl methylcellulose, methacrylic acid copolymer, methyl acrylate, methyl methacrylate, Opadry® beige, sugar spheres, talc, and triethyl citrate. Gelatin capsules contain gelatin, titanium dioxide, yellow iron oxide and edible inks. The 12.5 mg and 25 mg capsules also contain FD&C Blue #2. The 37.5 mg also contains red iron oxide. The 50 mg capsule also contains D&C Red #28, D&C Red #33, and FD&C Blue #1.

Distributed by:
Takeda Pharmaceuticals America, Inc., Cambridge, MA 02142

MYDAYIS is a registered trademark of Takeda Pharmaceuticals U.S.A., Inc.
OPADRY is a registered trademark of BPSI Holdings, LLC.
© 2025 Takeda Pharmaceuticals U.S.A., Inc. All rights reserved.

For more information about MYDAYIS go to www.mydayis.com or call 1-877-825-3327.

This Medication Guide has been approved by the U.S. Food and Drug Administration

MYD365

Revised: 3/2025

PRINCIPAL DISPLAY PANEL - 12.5 mg Capsule Bottle Label

ONCE-DAILY
NDC 54092-468-01

Mydayis®
(Mixed Salts of A Single-Entity
Amphetamine Product)

Extended-Release Capsules

12.5 mg

100 Capsules

Do not substitute for Adderall XR.

CII Rx only

Takeda

PRINCIPAL DISPLAY PANEL - 25 mg Capsule Bottle Label

ONCE-DAILY
NDC 54092-471-01

Mydayis®
(Mixed Salts of A Single-Entity
Amphetamine Product)

Extended-Release Capsules

25 mg

100 Capsules

Do not substitute for Adderall XR.

CII Rx only

Takeda

PRINCIPAL DISPLAY PANEL - 37.5 mg Capsule Bottle Label

ONCE-DAILY
NDC 54092-474-01

Mydayis®
(Mixed Salts of A Single-Entity
Amphetamine Product)

Extended-Release Capsules

37.5 mg

100 Capsules

Do not substitute for Adderall XR.

CII Rx only

Takeda

PRINCIPAL DISPLAY PANEL - 50 mg Capsule Bottle Label

ONCE-DAILY
NDC 54092-477-01

Mydayis®
(Mixed Salts of A Single-Entity
Amphetamine Product)

Extended-Release Capsules

50 mg

100 Capsules

Do not substitute for Adderall XR.

CII Rx only

Takeda